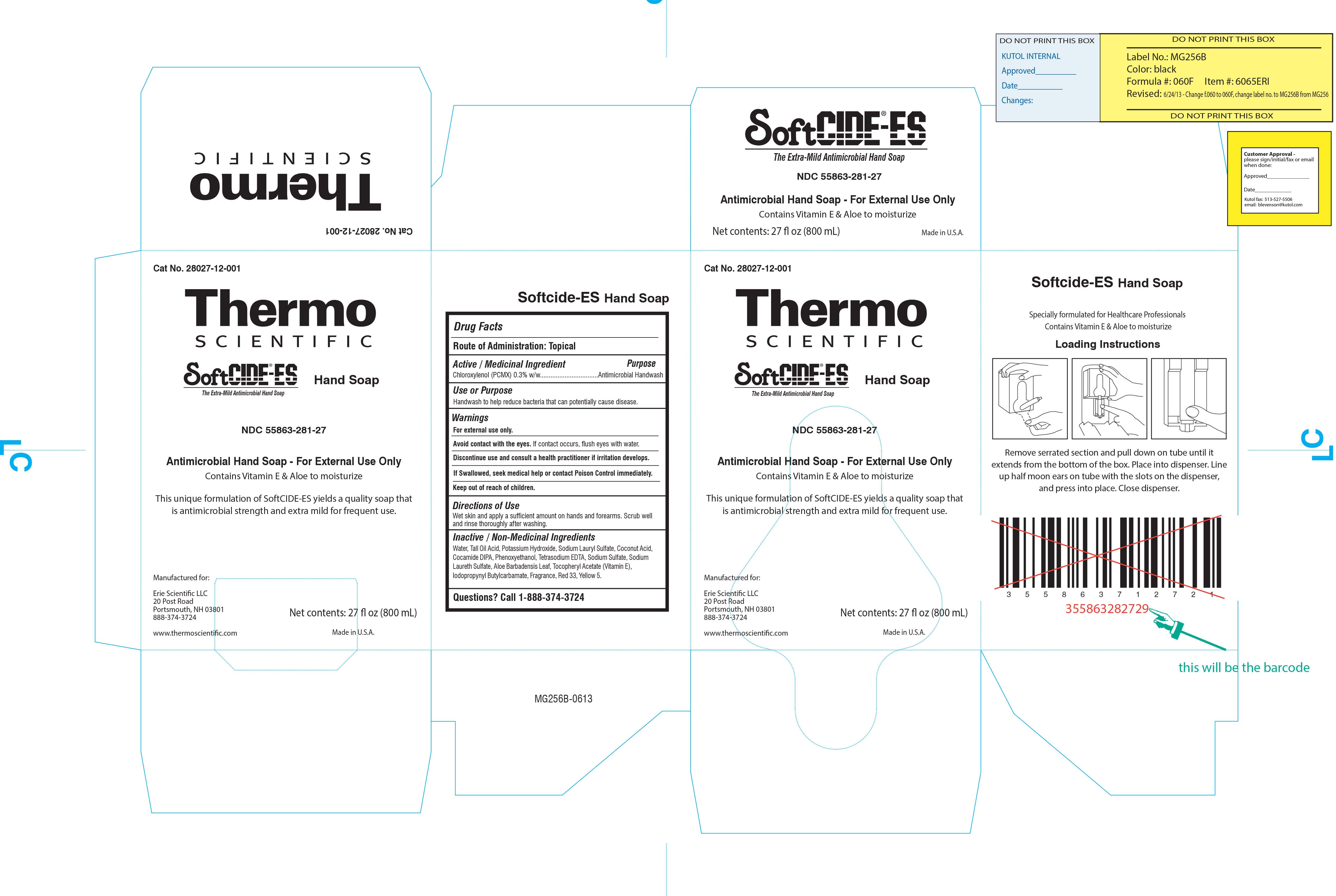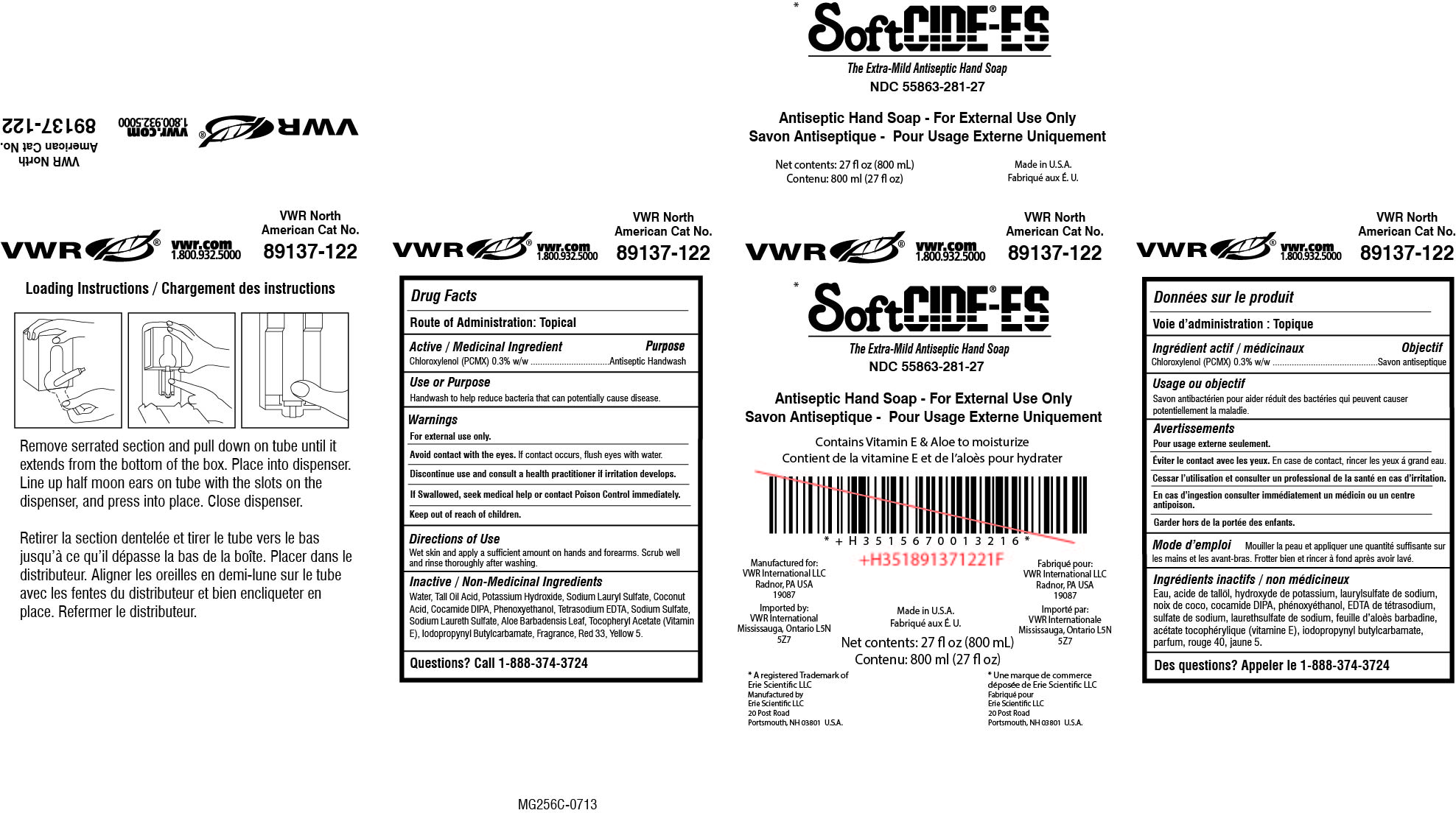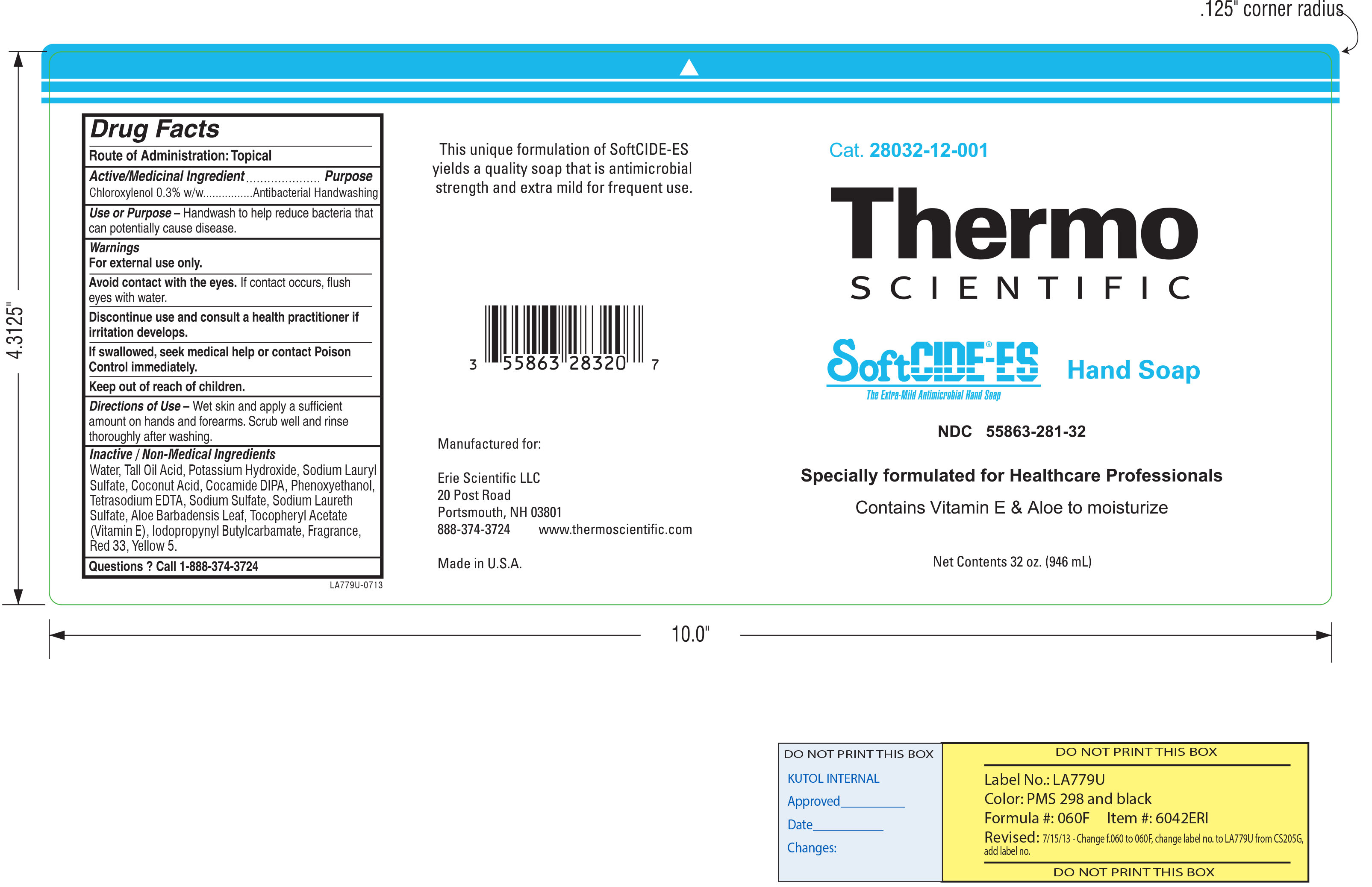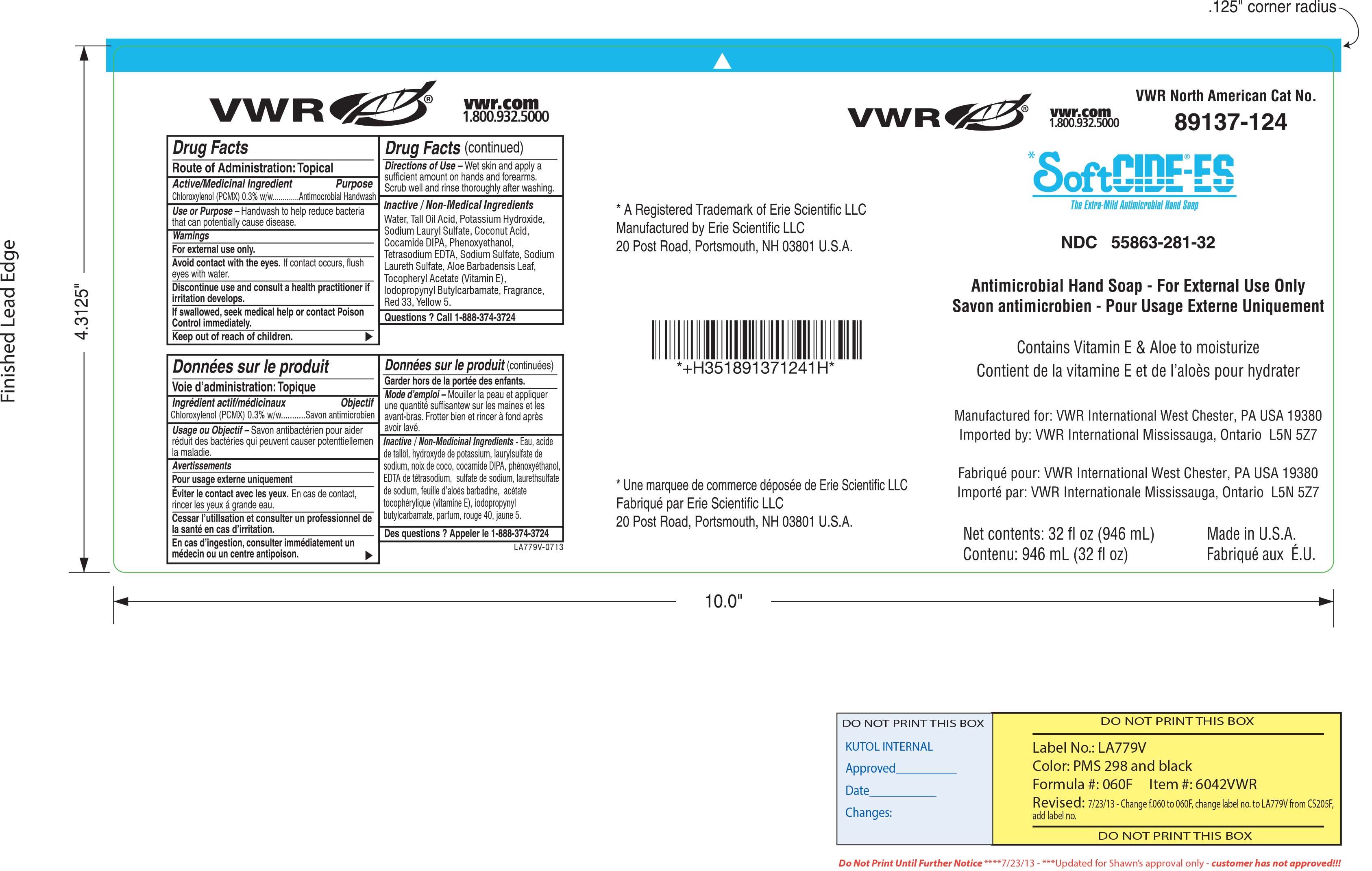 DRUG LABEL: SoftCIDE-ES
NDC: 55863-281 | Form: LIQUID
Manufacturer: Erie Scientific, LLC
Category: otc | Type: HUMAN OTC DRUG LABEL
Date: 20130723

ACTIVE INGREDIENTS: CHLOROXYLENOL 12.604 g/100 mL
INACTIVE INGREDIENTS: WATER; EDETATE SODIUM; POTASSIUM HYDROXIDE; TALL OIL; COCONUT ACID; SODIUM LAURYL SULFATE; COCO DIISOPROPANOLAMIDE; PHENOXYETHANOL; SODIUM SULFATE; SODIUM LAURETH SULFATE; ALOE VERA LEAF; .ALPHA.-TOCOPHEROL ACETATE, DL-; IODOPROPYNYL BUTYLCARBAMATE; D&C RED NO. 33; FD&C YELLOW NO. 5

SoftCIDE-ES

ACTIVE INGREDIENT

Chloroxylenol 0.3% w/w

INACTIVE INGREDIENT

Water, Tall Oil Acid, Potassium Hydroxide, Sodium Lauryl Sulfate, Coconut Acid, Cocamide DIPA, Phenoxyethanol, Tetrasodium EDTA, Sodium Sulfate, Sodium Laureth Sulfate, Aloe Barbadensis Leaf, Tocopheryl Acetate (Vitamin E Acetate), Iodopropynyl Butylcarbamate, Fragrance, Red 33, Yellow 5

DOSAGE AND ADMINISTRATION

Wet skin and apply a sufficient amount on hands and forearms. Scrub well and rinse thoroughly after washing.

PURPOSE

Handwash to help reduce bacteria that can potentially cause disease.

INDICATIONS AND USAGE

Handwash to help reduce bacteria that can potentially cause disease.

Avoid contact with the eyes. If contact occurs, flush eyes with water.

Discontinue use and consult a health practitioner if irritation develops. If swallowed seek medical help or contact Posion Control immediately. Keep out of reach of children.

Keep out of reach of children. If swallowed, seek medical help or contact Poison Control immediately.

WARNINGS

Avoid contact with eyes. If contact occurs, flush eyes with water.

For external use only.

Avoid contact with the eyes. If contact occurs, flush eyes with water.

Discontinue use and consult a health practitioner if irritation develops.

If swallowed seek medical help or contact Posion Control immediately.

Keep out of reach of children.

PACKAGE LABEL

55863-281-27-ERI.jpg

PACKAGE LABEL

55863-281-32-ERI.jpg

PACKAGE LABEL

55863-281-32-VWR.jpg

PACKAGE LABEL

55863-281-27-VWR.jpg